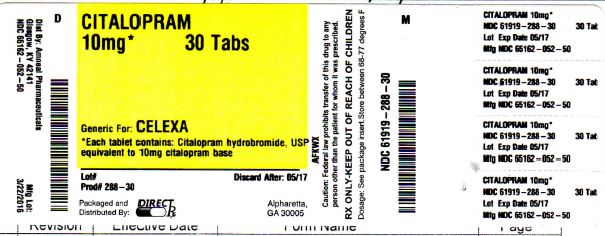 DRUG LABEL: CITALOPRAM
NDC: 61919-288 | Form: TABLET, FILM COATED
Manufacturer: DIRECT RX
Category: prescription | Type: HUMAN PRESCRIPTION DRUG LABEL
Date: 20160412

ACTIVE INGREDIENTS: CITALOPRAM HYDROBROMIDE 10 mg/1 1
INACTIVE INGREDIENTS: GLYCERIN; LACTOSE MONOHYDRATE; POLYVINYL ALCOHOL; TITANIUM DIOXIDE; FERRIC OXIDE YELLOW; FERRIC OXIDE RED; CELLULOSE, MICROCRYSTALLINE; STARCH, CORN; MAGNESIUM STEARATE; POLYETHYLENE GLYCOLS; SODIUM STARCH GLYCOLATE TYPE A POTATO; TALC; POVIDONE K12

CITALOPRAM 10mg 30 TABS